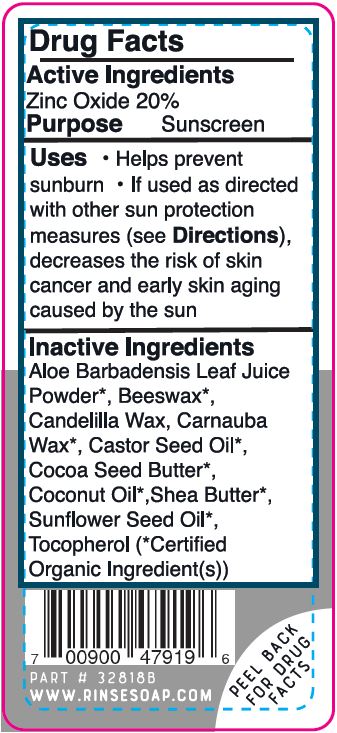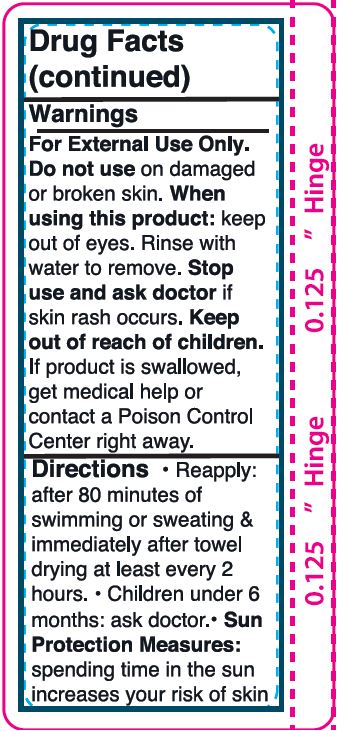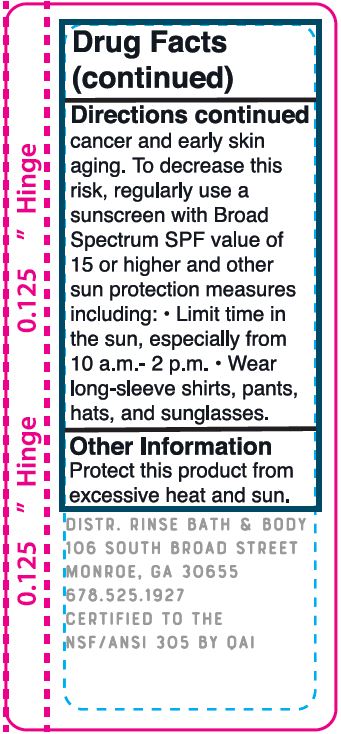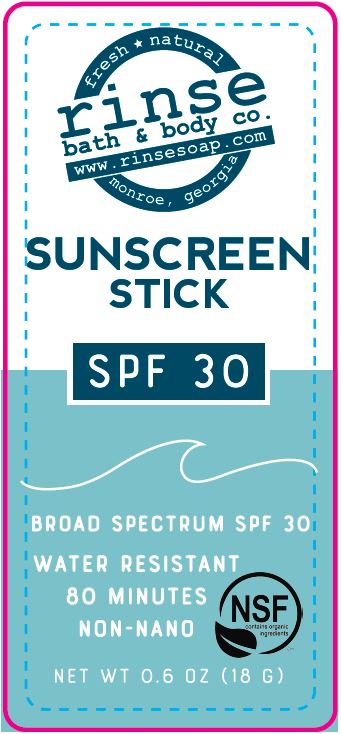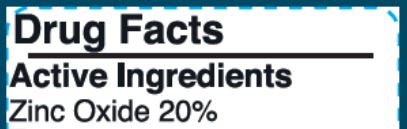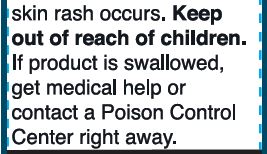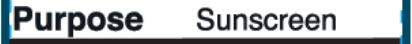 DRUG LABEL: Sunscreen
NDC: 62932-243 | Form: STICK
Manufacturer: Private Label Select Ltd CO
Category: otc | Type: HUMAN OTC DRUG LABEL
Date: 20201231

ACTIVE INGREDIENTS: ZINC OXIDE 20 g/100 g
INACTIVE INGREDIENTS: SUNFLOWER OIL; .ALPHA.-TOCOPHEROL, D-; COCONUT OIL; ALOE VERA LEAF; .GAMMA.-TOCOPHEROL; .DELTA.-TOCOPHEROL; SHEA BUTTER; WHITE WAX; CANDELILLA WAX; COCOA BUTTER; CARNAUBA WAX; CASTOR OIL; .BETA.-TOCOPHEROL

Rinse Bath & Body SPF 30 Unscented Sunstick